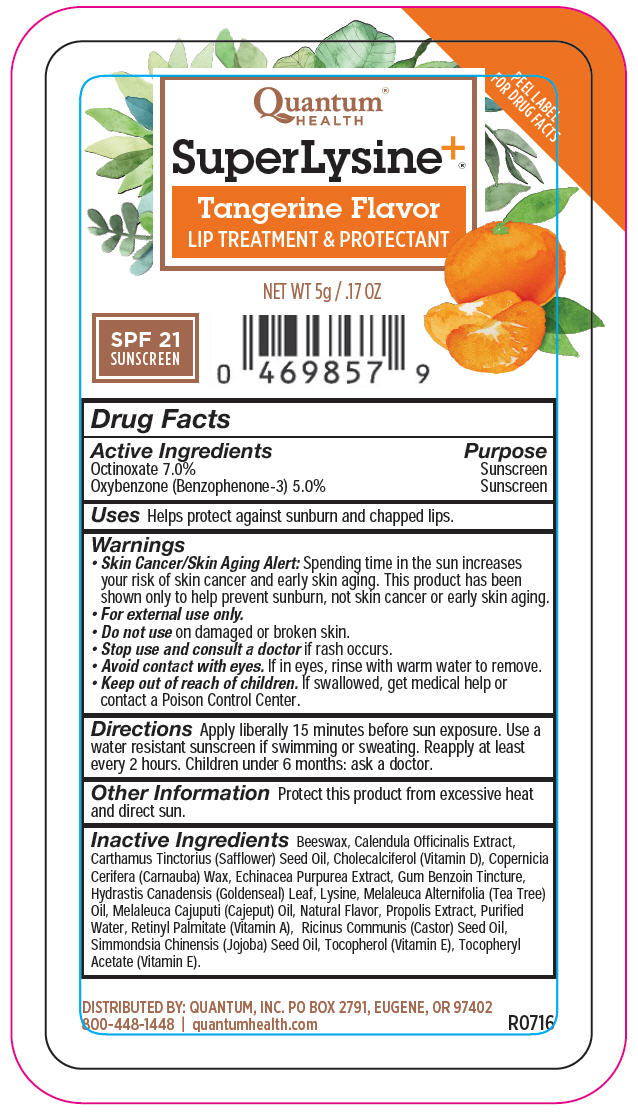 DRUG LABEL: Super Lysine Plus Tangerine Lip Treatment
NDC: 70084-230 | Form: LIPSTICK
Manufacturer: Quantum, Inc.
Category: otc | Type: HUMAN OTC DRUG LABEL
Date: 20251020

ACTIVE INGREDIENTS: OCTINOXATE 70 mg/1 g; OXYBENZONE 50 mg/1 g
INACTIVE INGREDIENTS: YELLOW WAX; CALENDULA OFFICINALIS FLOWER; ECHINACEA PURPUREA WHOLE; BENZOIN RESIN; GOLDENSEAL; LYSINE HYDROCHLORIDE; TEA TREE OIL; MELALEUCA CAJUPUTI LEAF OIL; PROPOLIS WAX; VITAMIN A PALMITATE; SAFFLOWER; CHOLECALCIFEROL; CARNAUBA WAX; WATER; CASTOR OIL; JOJOBA OIL; .ALPHA.-TOCOPHEROL ACETATE; TOCOPHEROL

Super Lysine^+®Tangerine Lip Treatment

Drug Facts

ACTIVE INGREDIENT

Active Ingredients | Purpose
Octinoxate 7.0% | Sunscreen
Oxybenzone (Benzophenone-3) 5.0% | Sunscreen

Uses

Helps protect against sunburn and chapped lips.

Warnings

- Skin Cancer/Skin Aging Alert:Spending time in the sun increases your risk of skin cancer and early skin aging. This product has been shown only to help prevent sunburn, not skin cancer or early skin aging.
- For external use only.

- Do not useon damaged or broken skin.

- Stop use and consult a doctorif rash occurs.
- Avoid contact with eyes.If in eyes, rinse with warm water to remove.

- Keep out of reach of children.If swallowed, get medical help or contact a Poison Control Center.

Directions

Apply liberally 15 minutes before sun exposure. Use a water resistant sunscreen if swimming or sweating. Reapply at least every 2 hours. Children under 6 months: ask a doctor.

Other Information

Protect this product from excessive heat and direct sun.

Inactive Ingredients

Beeswax, Calendula Officinalis Extract, Carthamus Tinctorius (Safflower) Seed Oil, Cholecalciferol (Vitamin D), Copernicia Cerifera (Carnauba) Wax, Echinacea Purpurea Extract, Gum Benzoin Tincture, Hydrastis Canadensis (Goldenseal) Leaf, Lysine, Melaleuca Alternifolia (Tea Tree) Oil, Melaleuca Cajuputi (Cajeput) Oil, Natural Flavor, Propolis Extract, Purified Water, Retinyl Palmitate (Vitamin A), Ricinus Communis (Castor) Seed Oil, Simmondsia Chinensis (Jojoba) Seed Oil, Tocopherol (Vitamin E), Tocopheryl Acetate (Vitamin E).

DISTRIBUTED BY: QUANTUM, INC. PO BOX 2791, EUGENE, OR 97402

PRINCIPAL DISPLAY PANEL - 5 g Cylinder Label

Quantum®
HEALTH

PEEL LABEL
FOR DRUG FACTS

SuperLysine^+®

Tangerine Flavor
LIP TREATMENT & PROTECTANT

NET WT 5g / .17 OZ

SPF 21
SUNSCREEN